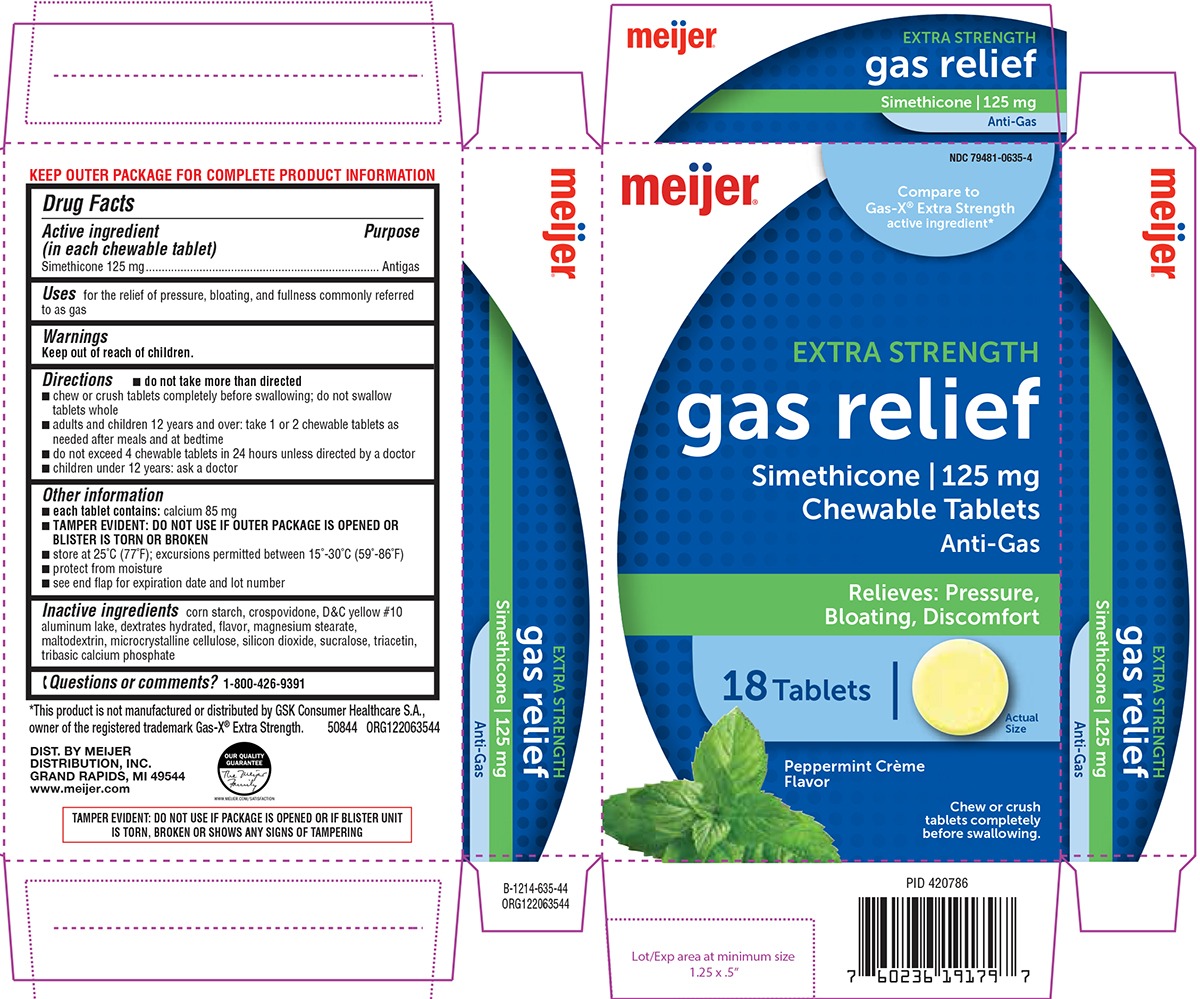 DRUG LABEL: Gas Relief
NDC: 79481-0635 | Form: TABLET, CHEWABLE
Manufacturer: Meijer Distribution, Inc.
Category: otc | Type: HUMAN OTC DRUG LABEL
Date: 20241204

ACTIVE INGREDIENTS: DIMETHICONE 125 mg/1 1
INACTIVE INGREDIENTS: STARCH, CORN; CROSPOVIDONE, UNSPECIFIED; D&C YELLOW NO. 10 ALUMINUM LAKE; DEXTROSE MONOHYDRATE; MAGNESIUM STEARATE; MALTODEXTRIN; MICROCRYSTALLINE CELLULOSE; SILICON DIOXIDE; SUCRALOSE; TRIACETIN; TRIBASIC CALCIUM PHOSPHATE; DIMETHICONE 410

Meijer 44-635

Active ingredient (in each chewable tablet)

Simethicone 125 mg

Purpose

Antigas

Uses

for the relief of pressure, bloating, and fullness commonly referred to as gas

Directions

- do not take more than directed
- chew or crush tablets completely before swallowing; do not swallow tablets whole
- adults and children 12 years and over: take 1 or 2 chewable tablets as needed after meals and at bedtime
- do not exceed 4 chewable tablets in 24 hours unless directed by a doctor
- children under 12 years: ask a doctor

Other information

- each tablet contains: calcium 85 mg
- TAMPER EVIDENT: DO NOT USE IF OUTER PACKAGE IS OPENED OR BLISTER IS TORN OR BROKEN
- store at 25°C (77°F); excursions permitted between 15°-30°C (59°-86°F)
- protect from moisture
- see end flap for expiration date and lot number

Inactive ingredients

corn starch, crospovidone, D&C yellow #10 aluminum lake, dextrates hydrated, flavor, magnesium stearate, maltodextrin, microcrystalline cellulose, silicon dioxide, sucralose, triacetin, tribasic calcium phosphate

Questions or comments?

1-800-426-9391

Principal Display Panel

meijer®

NDC 79481-0635-4

Compare to
Gas-X® Extra Strength
active ingredient*

EXTRA STRENGTH
gas relief
Simethicone | 125 mg
Chewable Tablets
Anti-Gas

Relieves: Pressure,
Bloating, Discomfort

18 Tablets

Actual
Size

Peppermint Crème
Flavor

Chew or crush
tablets completely
before swallowing.

TAMPER EVIDENT: DO NOT USE IF PACKAGE IS OPENED OR IF BLISTER UNIT
IS TORN, BROKEN OR SHOWS ANY SIGNS OF TAMPERING

*This product is not manufactured or distributed by GSK Consumer Healthcare S.A.,
owner of the registered trademark Gas-X® Extra Strength. 50844 ORG122063544

DIST. BY MEIJER
DISTRIBUTION, INC.
GRAND RAPIDS, MI 49544
www.meijer.com

Meijer 44-635